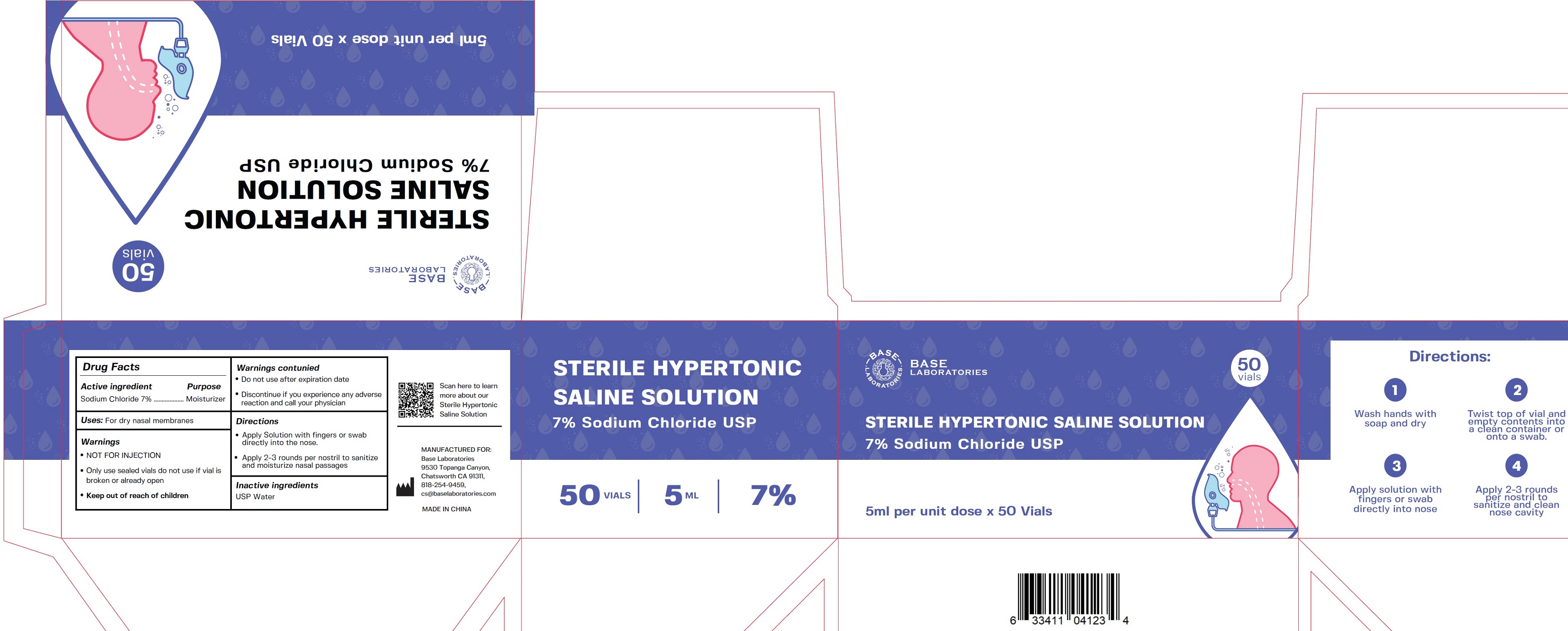 DRUG LABEL: Sterile Hypertonic Saline Solution 7 Sodium Chloride
NDC: 80327-009 | Form: LIQUID
Manufacturer: JOONEM LLC
Category: otc | Type: HUMAN OTC DRUG LABEL
Date: 20241223

ACTIVE INGREDIENTS: SODIUM CHLORIDE 70 mg/1 mL
INACTIVE INGREDIENTS: WATER

Sterile Hypertonic Saline Solution 7% Sodium Chloride USP

Active ingredient

Sodium Chloride 7%

Purpose

Moisturizer

Uses:

For dry nasal membranes

Warnings

- NOT FOR INJECTION
- Only use sealed vials do not use if vial is broken or already open

Keep out of reach of children

- Do not use after expiration date
- Discontinue if you experience any adverse reaction and call your physician

Directions

- Apply Solution with fingers or swab directly into the nose.
- Apply 2-3 rounds per nostril to sanitize and moisturize nasal passages

Inactive ingredients

USP Water